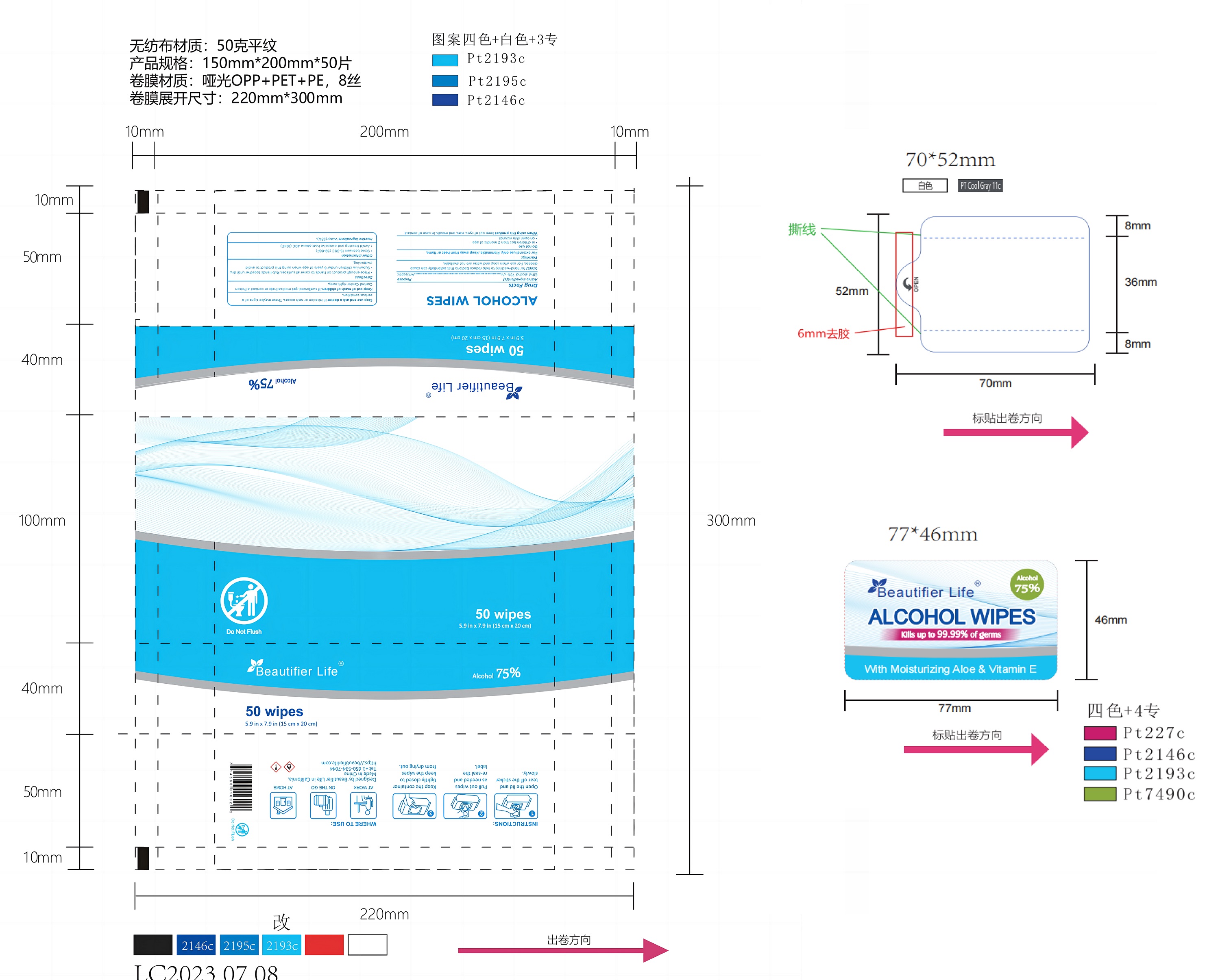 DRUG LABEL: Beautifier Life 75% Alcohol Wipes
NDC: 54860-404 | Form: CLOTH
Manufacturer: Shenzhen Lantern Science Co.,Ltd.
Category: otc | Type: HUMAN OTC DRUG LABEL
Date: 20240614

ACTIVE INGREDIENTS: ALCOHOL 75 mL/100 mL
INACTIVE INGREDIENTS: WATER 24.9 mL/100 mL; ALOE VERA LEAF 0.1 mL/100 mL

Beautifier Life 75% Alcohol Wipes

drug facts

Active ingredient

Active ingredient purpose

Ethyl alcohol 75%w/V Antiseptic

use

for hand-washing to help reduce bacteria that potentially can cause disesase.For use when soap and waterare not available.

warnings

For extermal use only.Flammable. Keep away from heat or flame.

Do not use

in children less than 2 months of age.

on open skin wounds.

When using this product

Keep out of eyes, ears ,and mouth.lIn case of contact

Stop use and ask a doctor

if iritation or rash occurs,these maybe signs of a serious condition.

Keep out of reach of children

if swallowed,get medical help or contact a Poison Control Center right away.

Directions

Place enough product on hands to cover all surfaces,Rub hands together until dry.
Supervise children under 6 years of age when using this product to avoid swallowing

Other information

Store between15-30C(59-86F)
Avoid freezing and excessive heat above 40C(104F)

Inactive ingredient

Water(25%)

Usage

Place enough product on hands to cover all surfaces.Rub hands together until dry.
Supervise children under 6 years of age when using this product to avoid swallowing.

package

Packaging